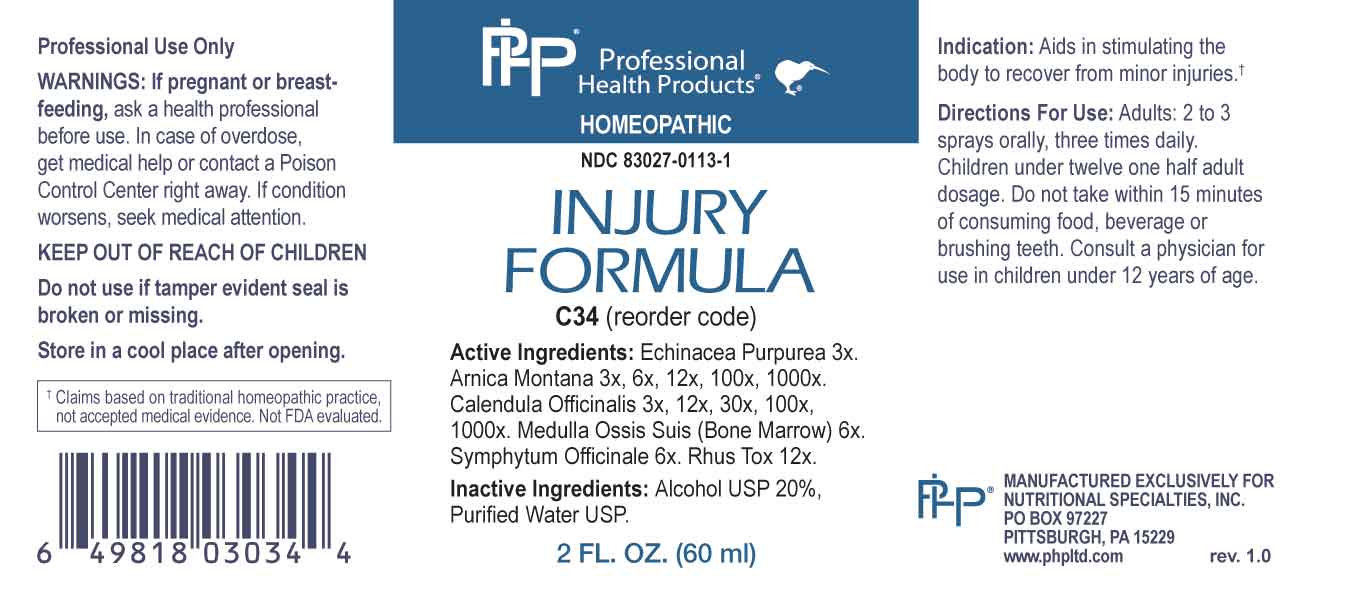 DRUG LABEL: Injury Formula
NDC: 83027-0113 | Form: SPRAY
Manufacturer: Nutritional Specialties, Inc.
Category: homeopathic | Type: HUMAN OTC DRUG LABEL
Date: 20231004

ACTIVE INGREDIENTS: ECHINACEA PURPUREA WHOLE 3 [hp_X]/1 mL; ARNICA MONTANA WHOLE 3 [hp_X]/1 mL; CALENDULA OFFICINALIS FLOWERING TOP 3 [hp_X]/1 mL; SUS SCROFA BONE MARROW 6 [hp_X]/1 mL; COMFREY ROOT 6 [hp_X]/1 mL; TOXICODENDRON PUBESCENS LEAF 12 [hp_X]/1 mL
INACTIVE INGREDIENTS: WATER; ALCOHOL

DRUG FACTS:

ACTIVE INGREDIENTS:

Echinacea Purpurea 3X, Arnica Montana 3X, 6X, 12X, 100X, 1000X, Calendula Officinalis 3X, 12X, 30X, 100X, 1000X, Medulla Ossis Suis (Bone Marrow) 6X, Symphytum Officinale 6X, Rhus Tox 12X.

PURPOSE:

Aids in stimulating the body to recover from minor injuries.†

†Claims based on traditional homeopathic practice, not accepted medical evidence. Not FDA evaluated.

WARNINGS:

Professional Use Only

If pregnant or breast-feeding, ask a health professional before use.

In case of overdose, get medical help or contact a Poison Control Center right away.

If condition worsens, seek medical attention.

KEEP OUT OF REACH OF CHILDREN

Do not use if tamper evident seal is broken or missing.

Store in a cool place after opening

KEEP OUT OF REACH OF CHILDREN:

In case of overdose, get medical help or contact a Poison Control Center right away.

DIRECTIONS:

Adults: 2 to 3 sprays orally, three times daily. Children under twelve one half adult dosage. Do not take within 15 minutes of consuming food, beverage or brushing teeth. Consult a physician for use in children under 12 years of age.

INDICATIONS:

Aids in stimulating the body to recover from minor injuries.†

†Claims based on traditional homeopathic practice, not accepted medical evidence. Not FDA evaluated.

INACTIVE INGREDIENTS:

Alcohol USP 20%, Purified Water USP.

QUESTIONS:

MANUFACTURED EXCLUSIVELY FOR

NUTRITIONAL SPECIALTIES, INC.

PO BOX 97227

PITTSBURG, PA 15229

www.phpltd.com

PACKAGE LABEL DISPLAY:

Professional

Health Products

HOMEOPATHIC

NDC 83027-0113-1

INJURY

FORMULA

2 FL. OZ (60 ml)